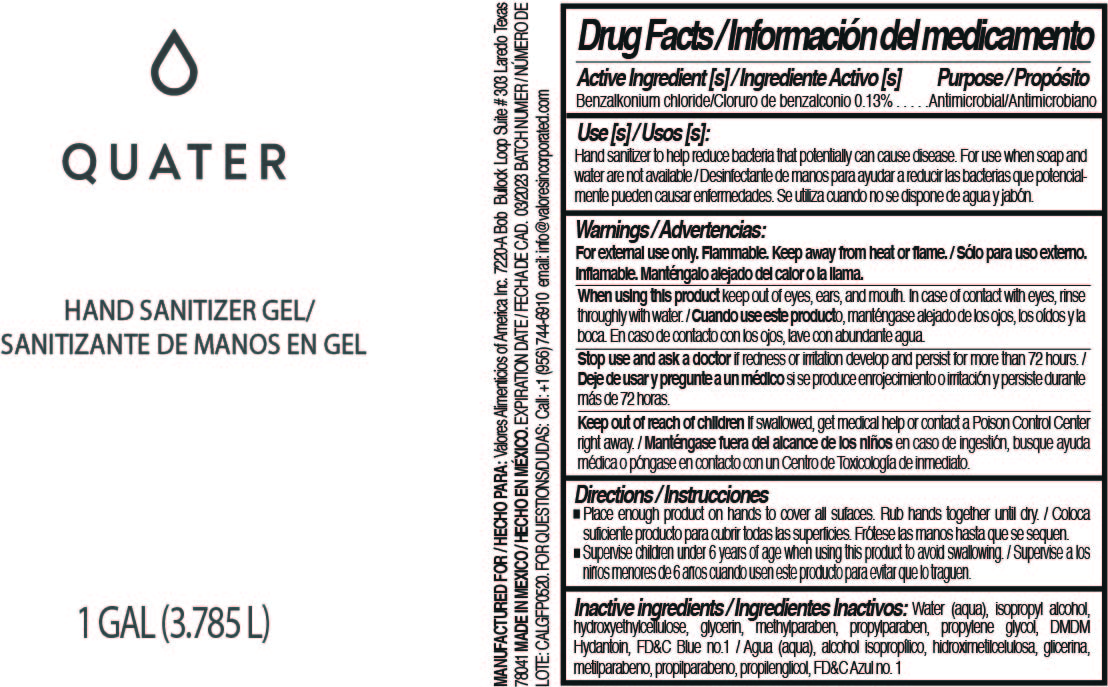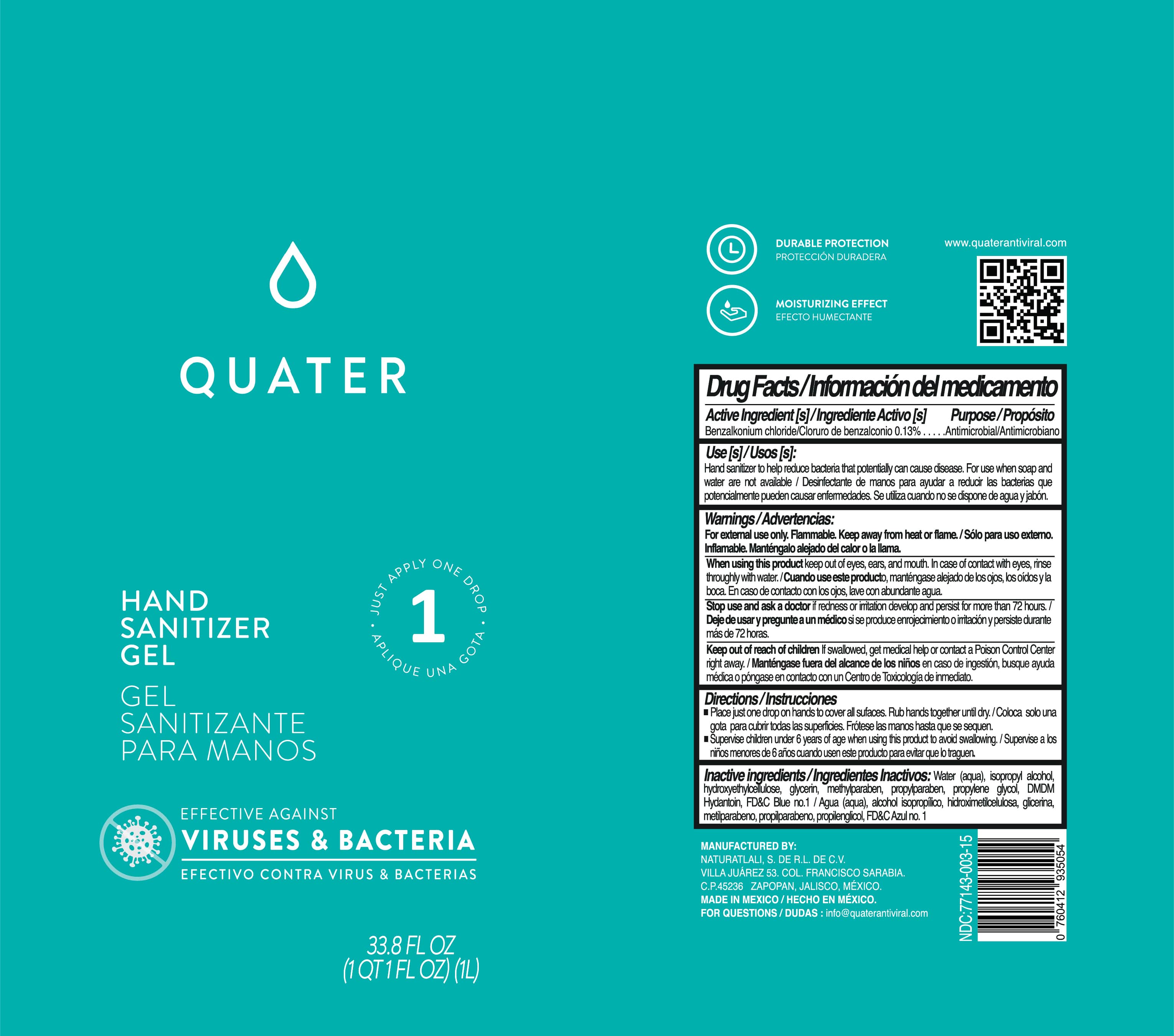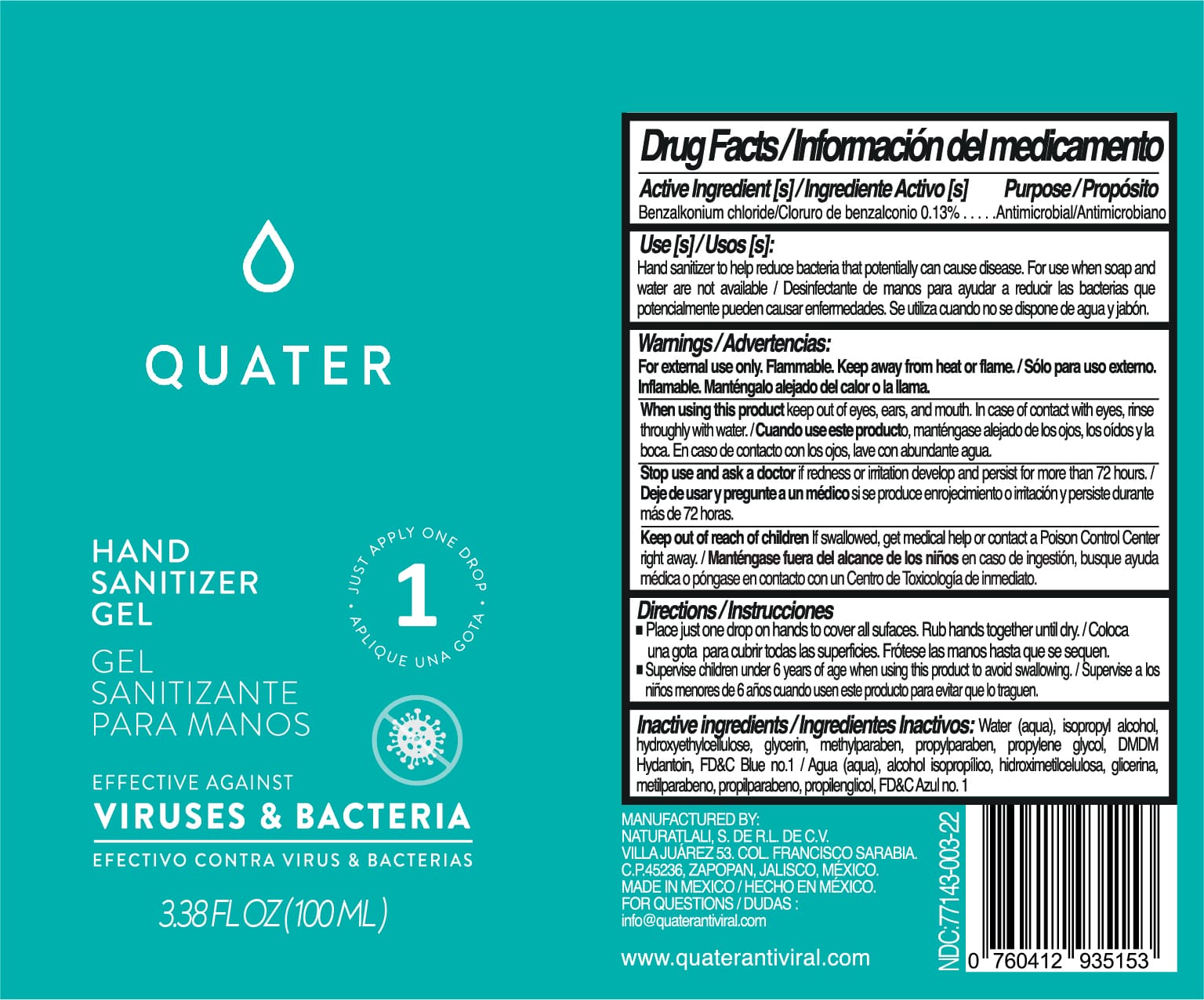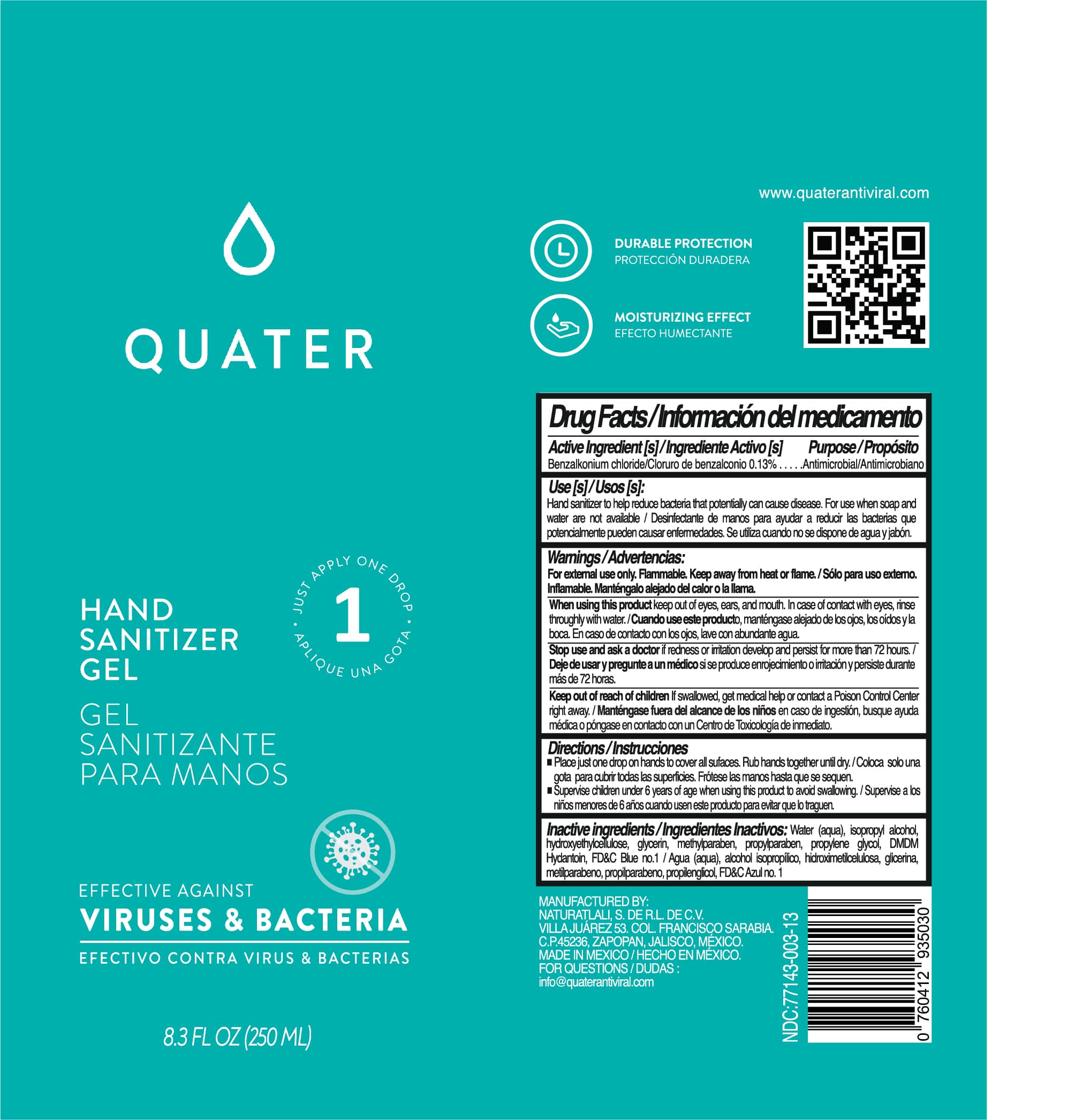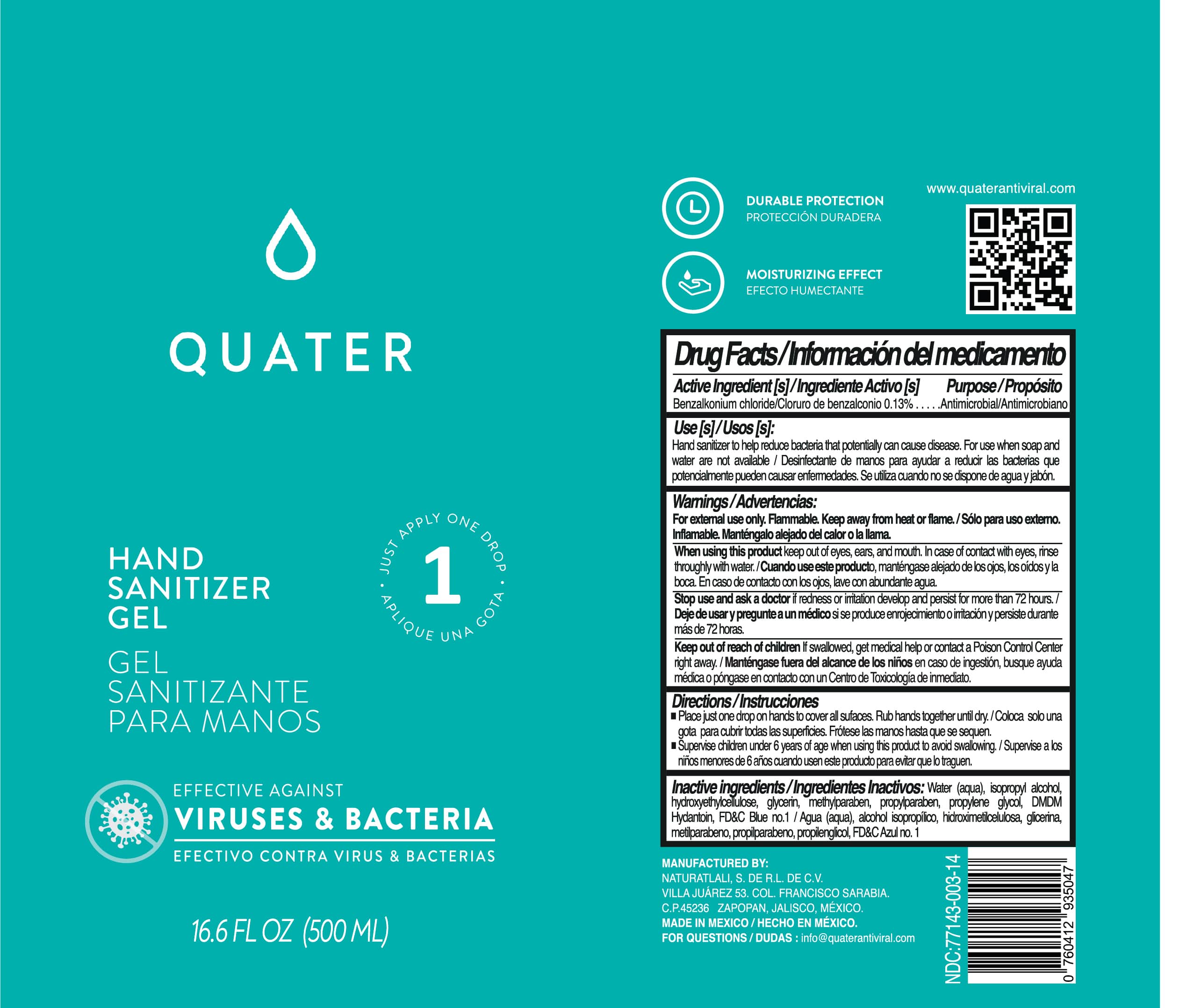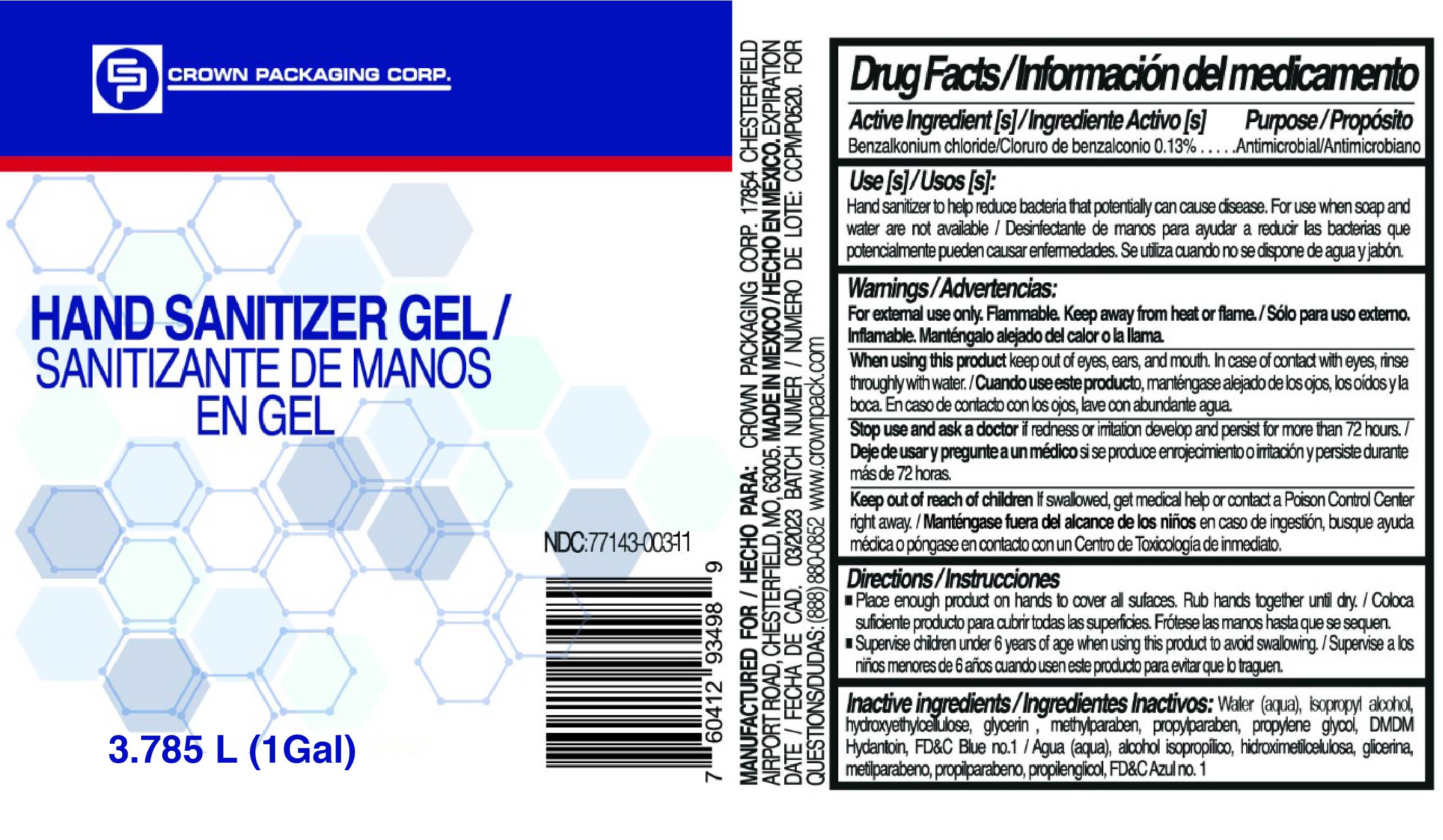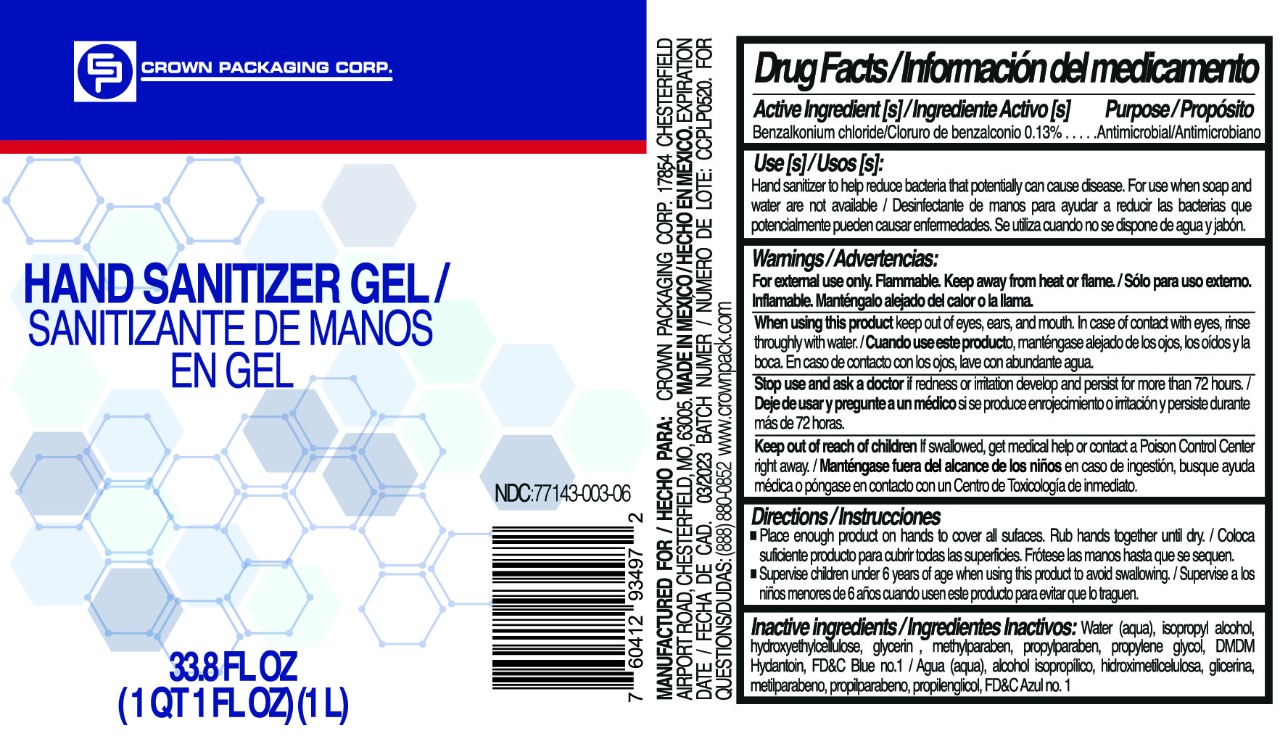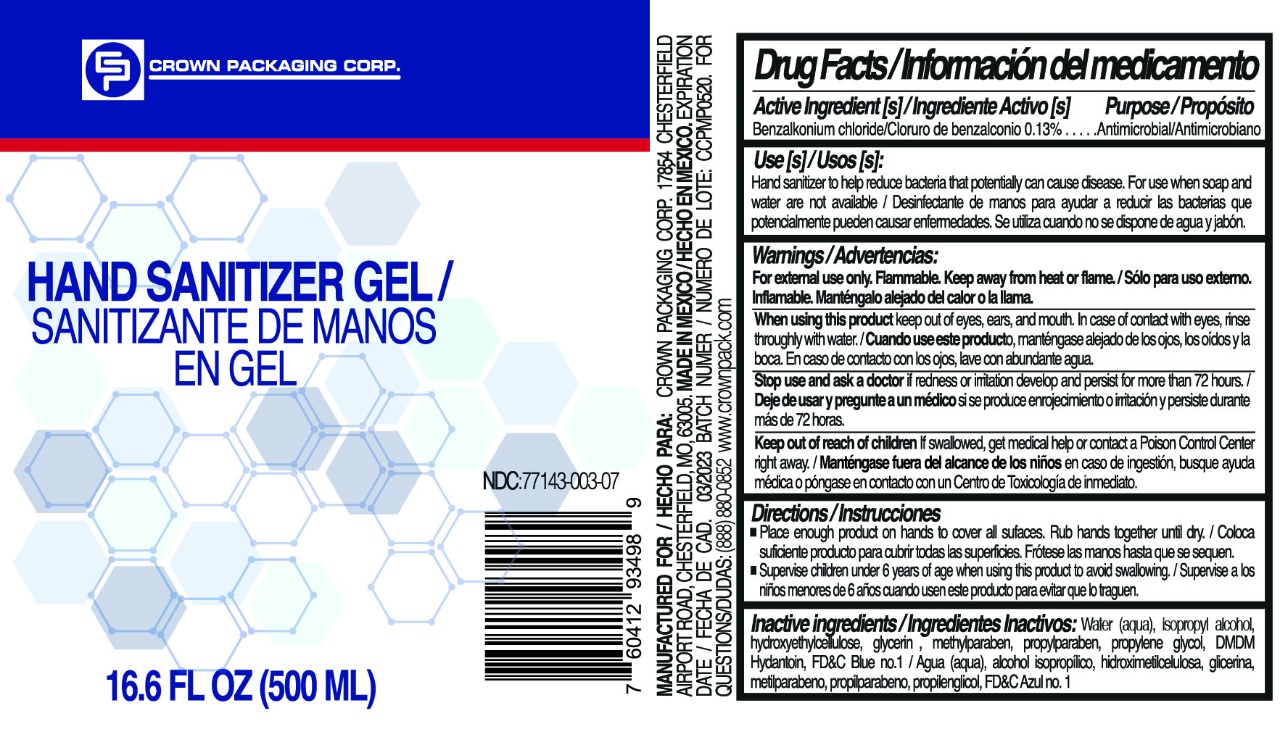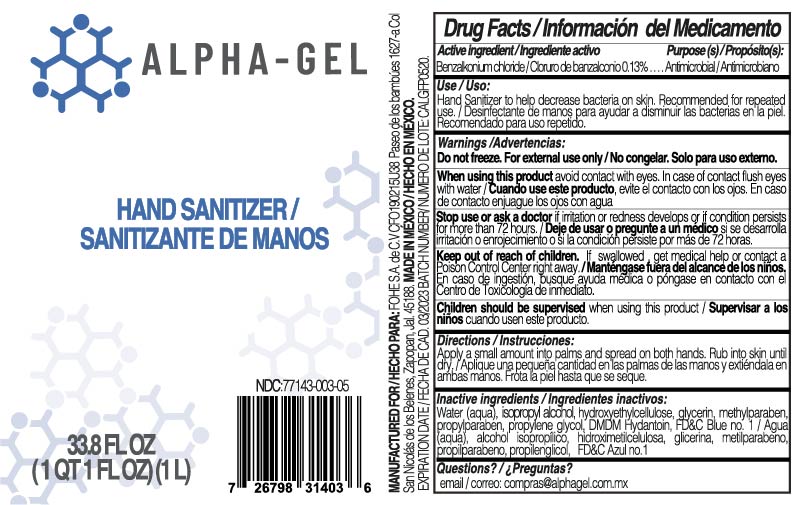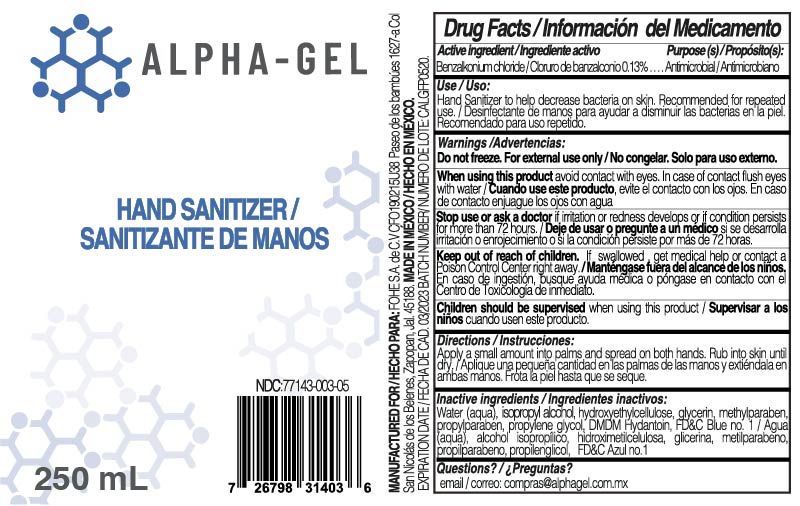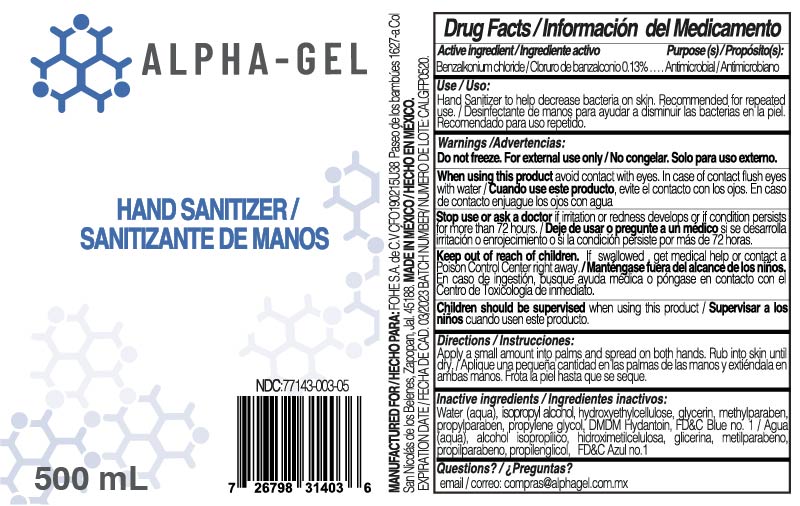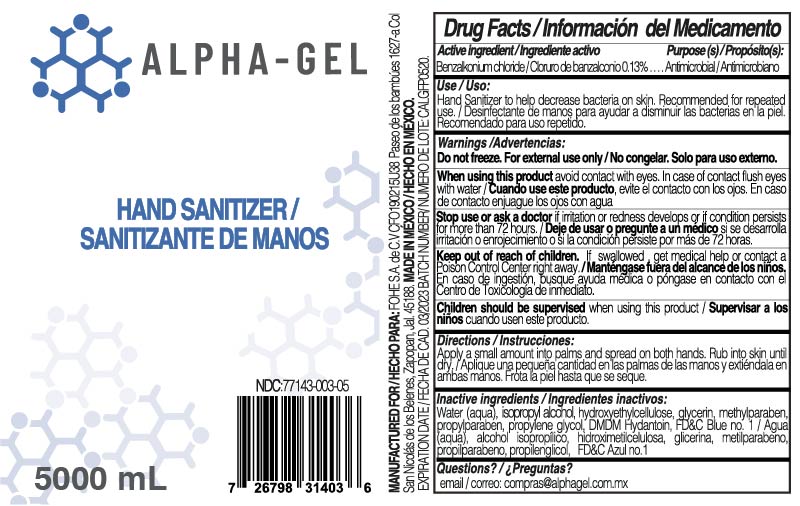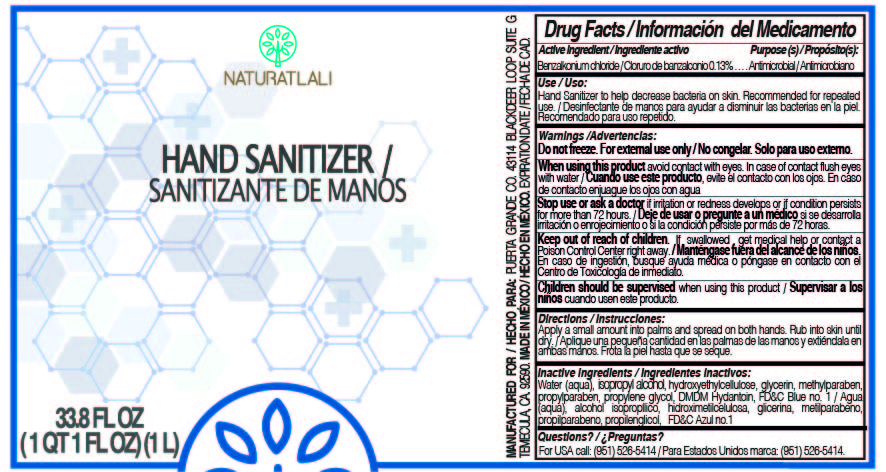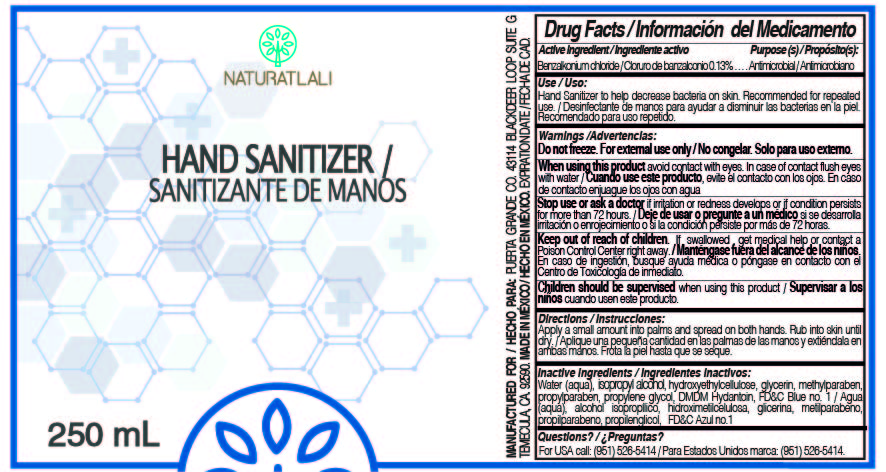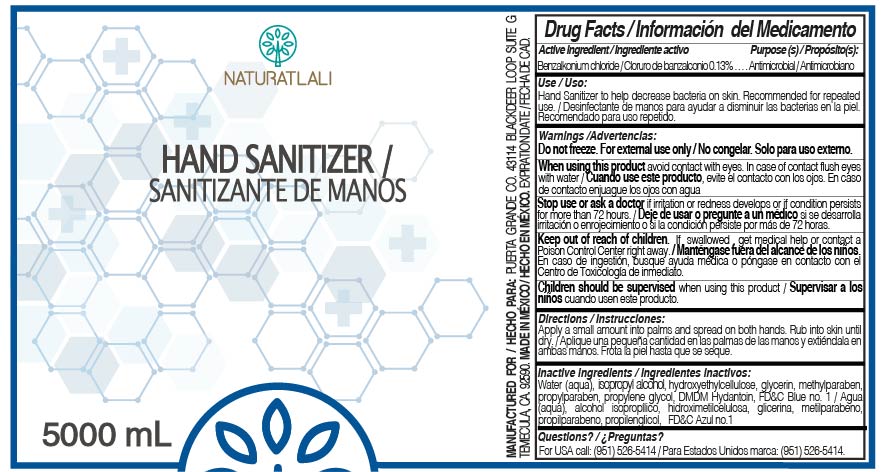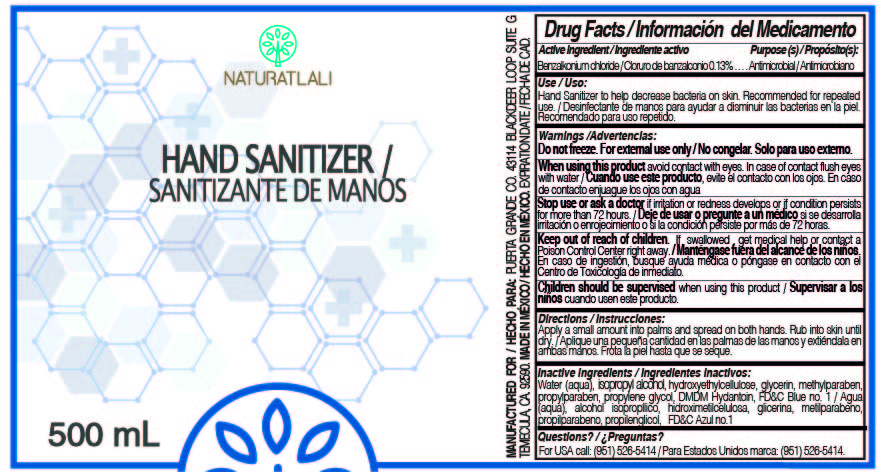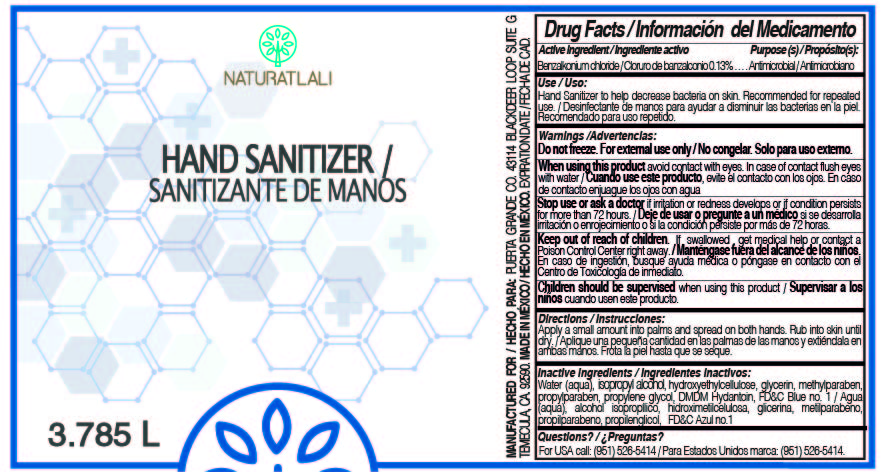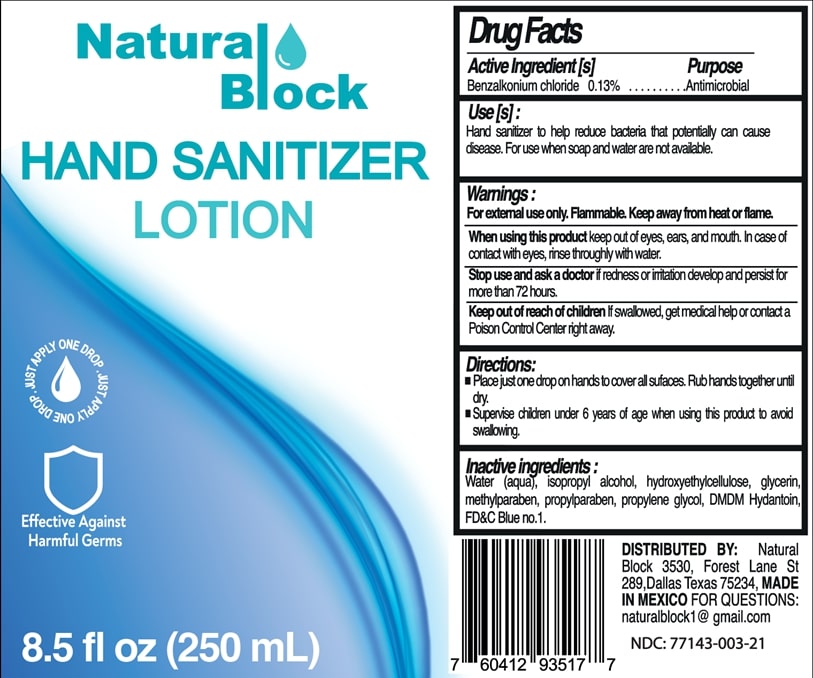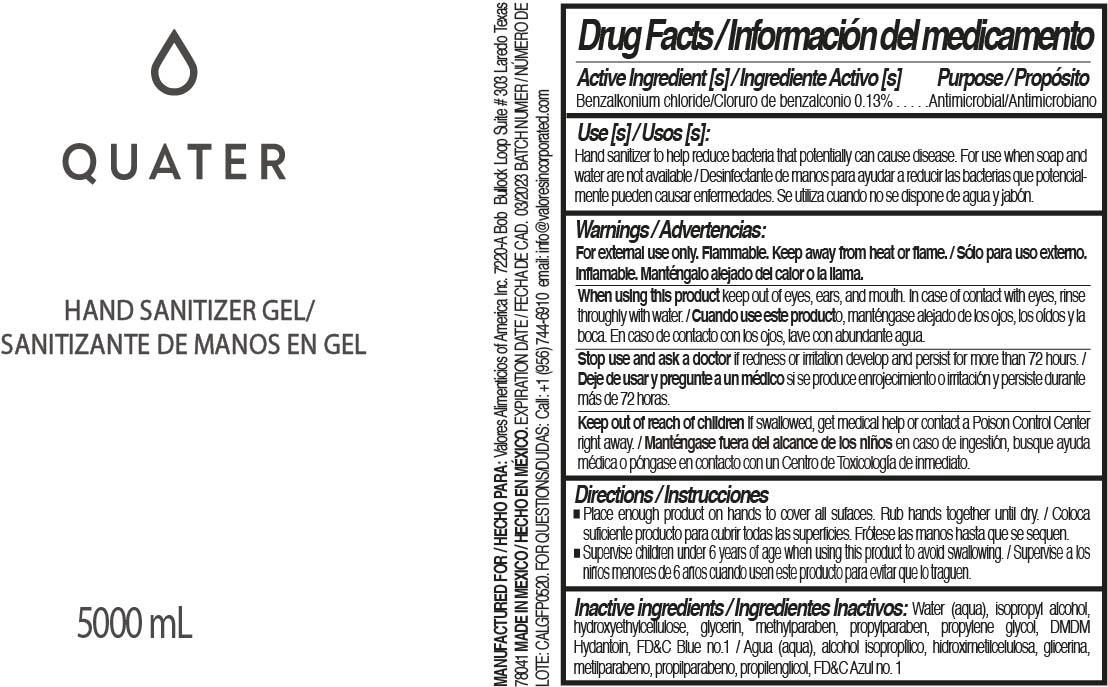 DRUG LABEL: Hand Sanitizer
NDC: 77143-003 | Form: GEL
Manufacturer: NATURATLALI S DE RL DE CV
Category: otc | Type: HUMAN OTC DRUG LABEL
Date: 20201123

ACTIVE INGREDIENTS: BENZALKONIUM CHLORIDE 0.13 g/100 mL
INACTIVE INGREDIENTS: ISOPROPYL ALCOHOL 10 mL/100 mL; GLYCERIN 0.25 mL/100 mL; HYDROXYETHYL CELLULOSE (100 MPA.S AT 2%) 0.01 g/100 mL; WATER; METHYLPARABEN 0.025 g/100 mL; PROPYLPARABEN 0.025 g/100 mL; DMDM HYDANTOIN 0.025 g/100 mL; FD&C BLUE NO. 1 0.001 g/100 mL; DIPROPYLENE GLYCOL 0.025 mL/100 mL

Active Ingredient(s)

Benzalkonium Chloride 0.13% w/v. Purpose: Antiseptic

Purpose

Antiseptic, Hand Sanitizer

Use

Hand Sanitizer to help reduce bacteria that potentially can cause disease. For use when soap and water are not available.

Warnings

For external use only.

Do not use

- on open wounds

When using this product keep out of eyes, ears, and mouth. In case of contact with eyes, rinse eyes thoroughly with water.
Stop use and ask a doctor if irritation or rash occurs. These may be signs of a serious condition.
Keep out of reach of children. If swallowed, get medical help or contact a Poison Control Center right away.

Stop use and ask a doctor if irritation or rash occurs. These may be signs of a serious condition.

Keep out of reach of children. If swallowed, get medical help or contact a Poison Control Center right away.

Directions

- Place enough product on hands to cover all surfaces. Rub hands together until dry.
- Supervise children under 6 years of age when using this product to avoid swallowing.

Other information

- Store between 15-30C (59-86F)
- Avoid freezing and excessive heat above 40C (104F)

Inactive ingredients

water, isopropyl alcohol, hydroxyethyl cellulose, glycerin, methylparabene, propylparabene, propylene glycol, DMDM Hydantoin, FD&C Blue No 1

Package Label - Principal Display Panel

1000 mL NDC: 77143-003-01

500 mL NDC: 77143-003-02

250 mL NDC: 77143-003-03

5000 mL NDC: 77143-003-04

1000 mL NDC: 77143-003-05

1000 mL NDC: 77143-003-06

500 mL NDC: 77143-003-07

500 mL NDC: 77143-003-08

250 mL NDC: 77143-003-09

5000 mL NDC: 77143-003-10

3785 mL NDC: 77143-003-11

5000 mL NDC: 77143-003-12

250 mL NDC: 77143-003-13

500 mL NDC: 77143-003-14

1000 mL NDC: 77143-003-15

3785 mL NDC: 77143-003-16

3785 mL NDC: 77143-003-17

100 mL NDC: 77143-003-22

250 mL NDC: 77143-003-21